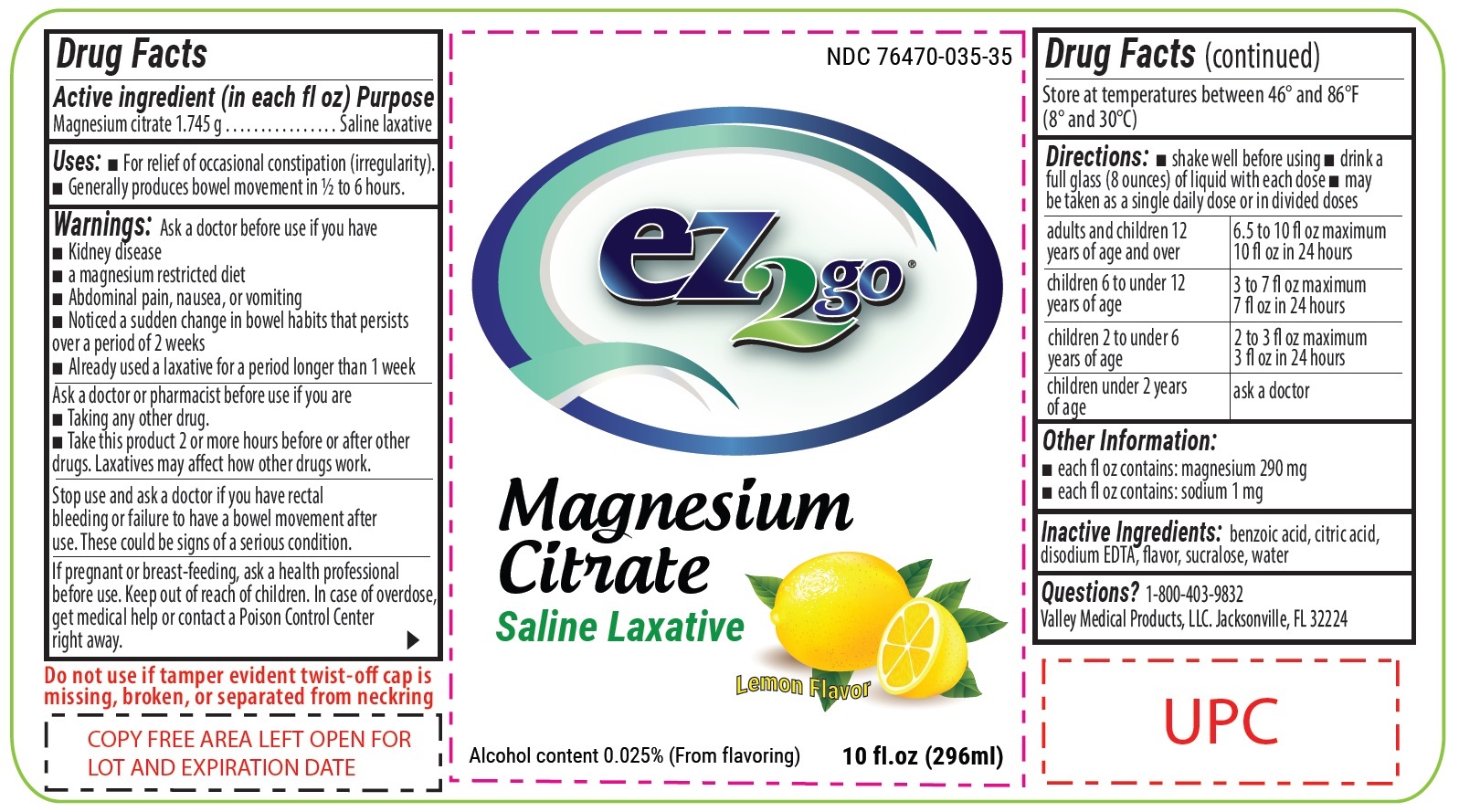 DRUG LABEL: EZ2Go Magnesium Citrate Saline Laxative Lemon Flavor
NDC: 76470-025 | Form: LIQUID
Manufacturer: Valley Medical Products LLC
Category: otc | Type: HUMAN OTC DRUG LABEL
Date: 20240131

ACTIVE INGREDIENTS: MAGNESIUM CITRATE 1.745 g/1 mL
INACTIVE INGREDIENTS: BENZOIC ACID; CITRIC ACID MONOHYDRATE; EDETATE DISODIUM ANHYDROUS; SUCRALOSE; WATER

EZ2Go Magnesium Citrate Saline Laxative Lemon Flavor

Active ingredient (in each fl oz)

Magnesium citrate 1.745 g

Purpose

Saline laxative

Uses

- For relief of occasional constipation (irregularity).
- Generally produese bowel movement in 1/2 to 6 hours.

Warnings:

Ask a doctor before use if you have

- Kidney disease
- a magnesium restricted diet
- Abdominal pain, nausea, or vomting
- Noticed a sudden change in bowel habits that persists over a period of 2 weeks
- Already used a laxative for a period longer than 1 week

Ask a doctor or pharmacits before use if you are

- Taking any other drug.
- Take this product 2 or more hours before or after other drugs. Laxatives may affect how other drugs work.

Stop use and ask a doctor

if you have rectal bleeding or failure to have a bowel movement after use. These could be signs of a serious condition.

If pregnant or breast-feeding,

ask a health professional before use.

Keep out of reach of children.

In case of overdose, get medical help or contact Poison Control Centre right away. Store at temparatue between 46º and 86º F (8º and 30º)

Directions

- shake well before using
- drink a full glass (8 ounces) of liquid with each dose
- may be taken as a single daily dose or in divided doses

adults and children 12 years of age and over | 6.5 to 10 fl oz maximum 10 fl oz in 24 hours
children 6 to under 12 years of age | 3 to 7 fl oz maximum 7 fl oz in 24 hours
children 2 to under 6 years of age | 2 to 3 fl oz maximum 3 fl oz in 24 hours
children under 2 years of age | ask a doctor

Other Information:

- each fl oz contains: magnesium 290 mg
- each fl oz contains: sodium 1 mg

Inactive Ingredients:

benzoic acid, citric acid, disodium EDTA, flavor, sucralose, water

Questions?

1-800-403-9832 Valley Medical Products, LLC, Jacksoville, FL 32224